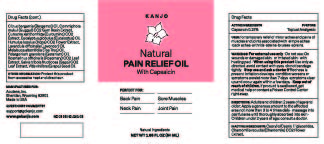 DRUG LABEL: Kanjo Natural Pain relief oil
NDC: 35192-040 | Form: OIL
Manufacturer: CA-BOTANA INTERNATIONAL
Category: otc | Type: HUMAN OTC DRUG LABEL
Date: 20241105

ACTIVE INGREDIENTS: CAPSAICIN 0.075 g/50 g
INACTIVE INGREDIENTS: GUGGUL; EUCALYPTUS OIL; ROSEMARY OIL; CURCUMA XANTHORRHIZA OIL; HOPS OIL; TEA TREE OIL; PELARGONIUM GRAVEOLENS FLOWER OIL; SAGE OIL; GRAPEFRUIT; CHAMOMILE; MEDIUM-CHAIN TRIGLYCERIDES; BERGAMOT OIL

Kanjo oil Pain Natural Relief

Warning section

For external use only.
Do not use on wounds or damaged skin
When using this product: use only as directed. Avoid contact with eyes. Do no bandage tightly
Stop use and ask a doctor if: redness is present. Irritation develops. Condition worsens or symptoms persist more than 7 days. Symptoms clear up and occur again within a few days.
Store at room temperature. Lot number and expiration date see crimp or see box.

OTC - Active Ingredient

Capsaicin 0.15%

Purpose

For temporary relief of minor aches and paims of muscles and joints associated with *single aches *back aches *arthritis * strains* bruises*sprains

Keep out of reach of children. If swallowed get medical help or contact a Posion Control Center immediately.

Inactive Ingredients

Capri/ capri /tryglyceride, Chamomilla recutita (Chamomile) flower, Citrus bergamia (Bergamot) oil, Commiphora mukul (Guggul) Gum resin, Curcuma Xanthorrhiza,Eucaliptus globulus (Eucaliptus) oil,Humulus lupulus (Hop), Lavandula officinalis(Lavender) oil, Melaleuca alternifolia (Tea tree) oil, Pelargonium gravolens (Geranium) oil, Rosmarinus officinalis (Rosemary), Sage Triloba Fructicosa (Salvia triloba (Sage), Vitis vinifera (Grape seed)oil

Dosage & Administration

External topical analgesic, massage oil to the affected area not more than 4 times daily

Indications & Usage

Apply generous amont of oil directly on affected area. Massage into painful area until thoroughly absorbed into skin